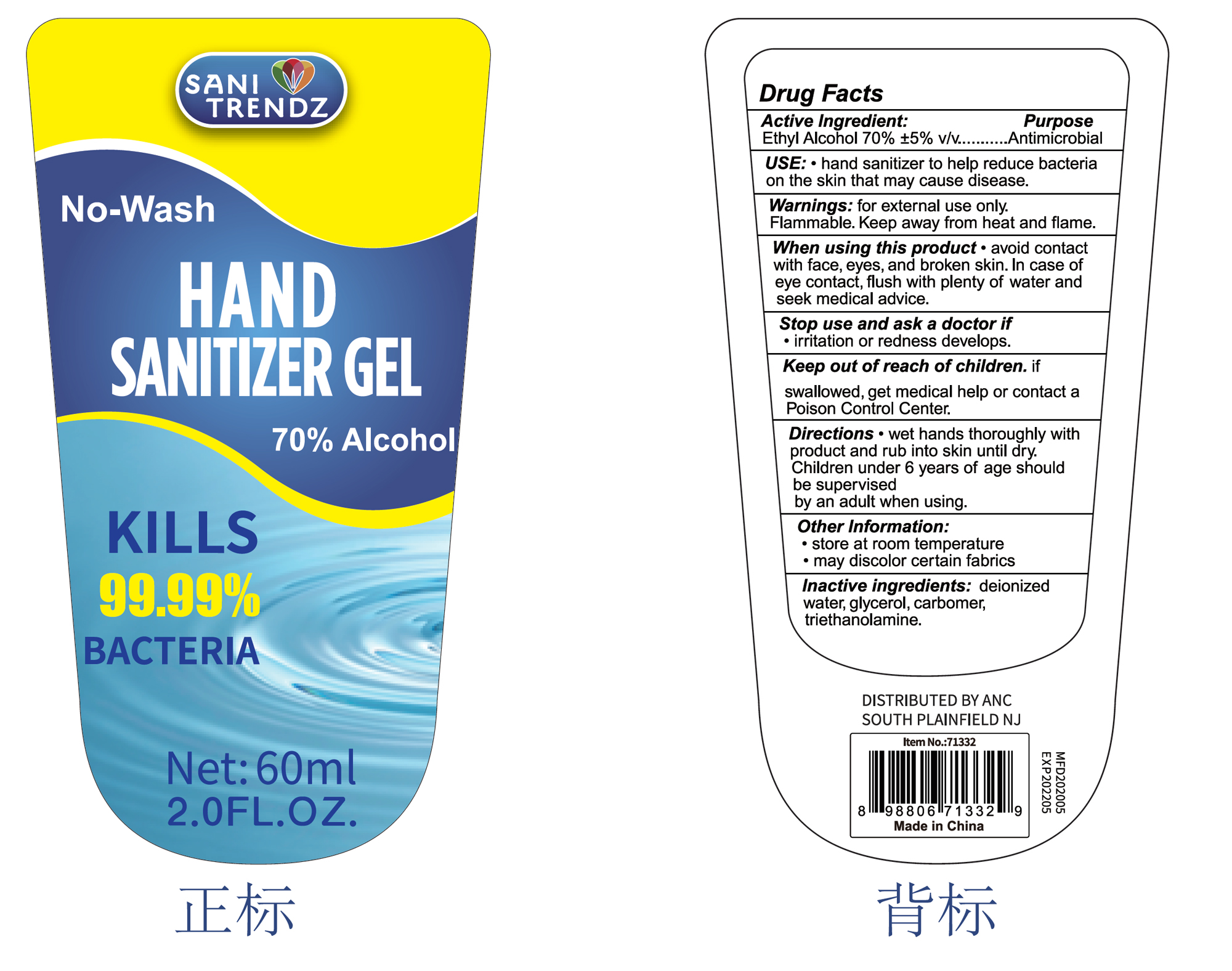 DRUG LABEL: 70% alcohol hand sanitzer
NDC: 75021-003 | Form: GEL
Manufacturer: D Zone Imports, Llc
Category: otc | Type: HUMAN OTC DRUG LABEL
Date: 20200625

ACTIVE INGREDIENTS: ALCOHOL 70 mL/100 mL
INACTIVE INGREDIENTS: GLYCERIN; TROLAMINE; WATER; CARBOMER HOMOPOLYMER, UNSPECIFIED TYPE

70% alcohol hand sanitzer

Active Ingredient(s)

Alcohol 70% v/v. Purpose: Antiseptic

Purpose

Antiseptic, Hand Sanitizer

Use

Hand Sanitizer to help reduce bacteria that potentially can cause disease.

Warnings

For external use only. Flammable. Keep away from heat or flame

When using this product

Avoid contact with face, eyes, and broken skin. In case of eye contact, flush with plenty of water and seek medical advice.

Stop use and ask a doctor if

irritation or redness develops

Keep out of reach of children.

If swallowed, get medical help or contact a Poison Control Center.

Directions

- Wet hands thoroughly with product and rub into skin until dry.
- Children under 6 years of age should be supervised by an adult when using.

Other information

- Store at room temperature
- May discolor certain fabrics

Inactive ingredients

Deionized Water, Glycerol, Carbopol, Triethanolamine

Package Label - Principal Display Panel

60 mL NDC: 75021-003-01